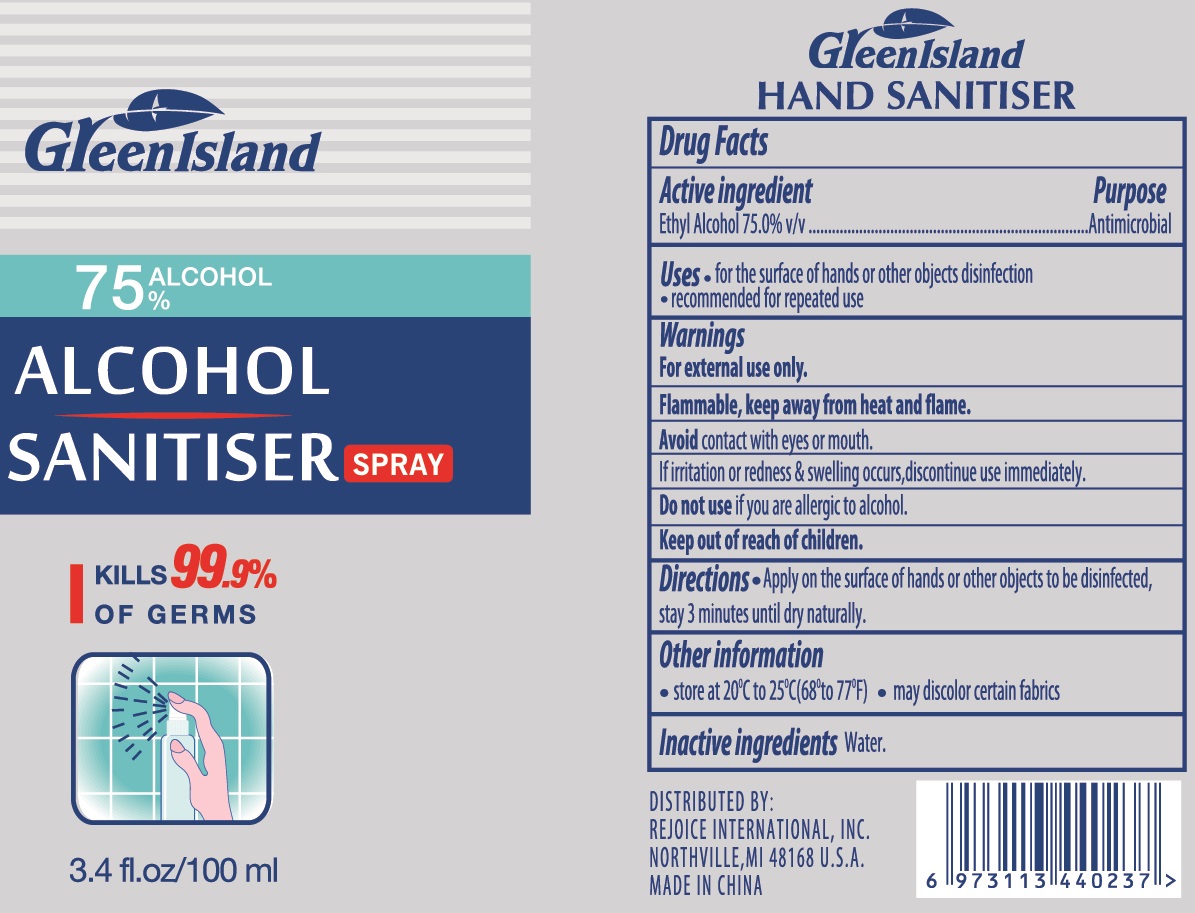 DRUG LABEL: Green Island
NDC: 75742-002 | Form: GEL
Manufacturer: Zhejiang Guoyao Jingyue Aerosol Co., Ltd.
Category: otc | Type: HUMAN OTC DRUG LABEL
Date: 20260105

ACTIVE INGREDIENTS: ALCOHOL 75 mL/100 mL
INACTIVE INGREDIENTS: TROLAMINE; ALOE VERA LEAF; GLYCERIN; CARBOMER 940; WATER; .ALPHA.-TOCOPHEROL

Green Island Hand Sanitizer

Active ingredient

Ethyl Alcohol 75% v/v.

Purpose

Antimicrobial

Uses

- for the surface of hands or other objects disinfection
- recommended for repeated use

Warnings

For external use only.

Flammable, keep away from heat or flame

Avoid contact with eyes or mouth.

If irritation or redness & swelling occurs, discontinue use immediately.

Do not use

if you are allergic to alcohol

Keep out of reach of children.

Directions

- Apply on the surface of hands or other objects to be disinfected, stay 3 minutes until dry naturally.

Other information

- Store at 20ºC to 25ºC (68º to 77ºF)
- may discolor certain fabrics

Inactive ingredients

water